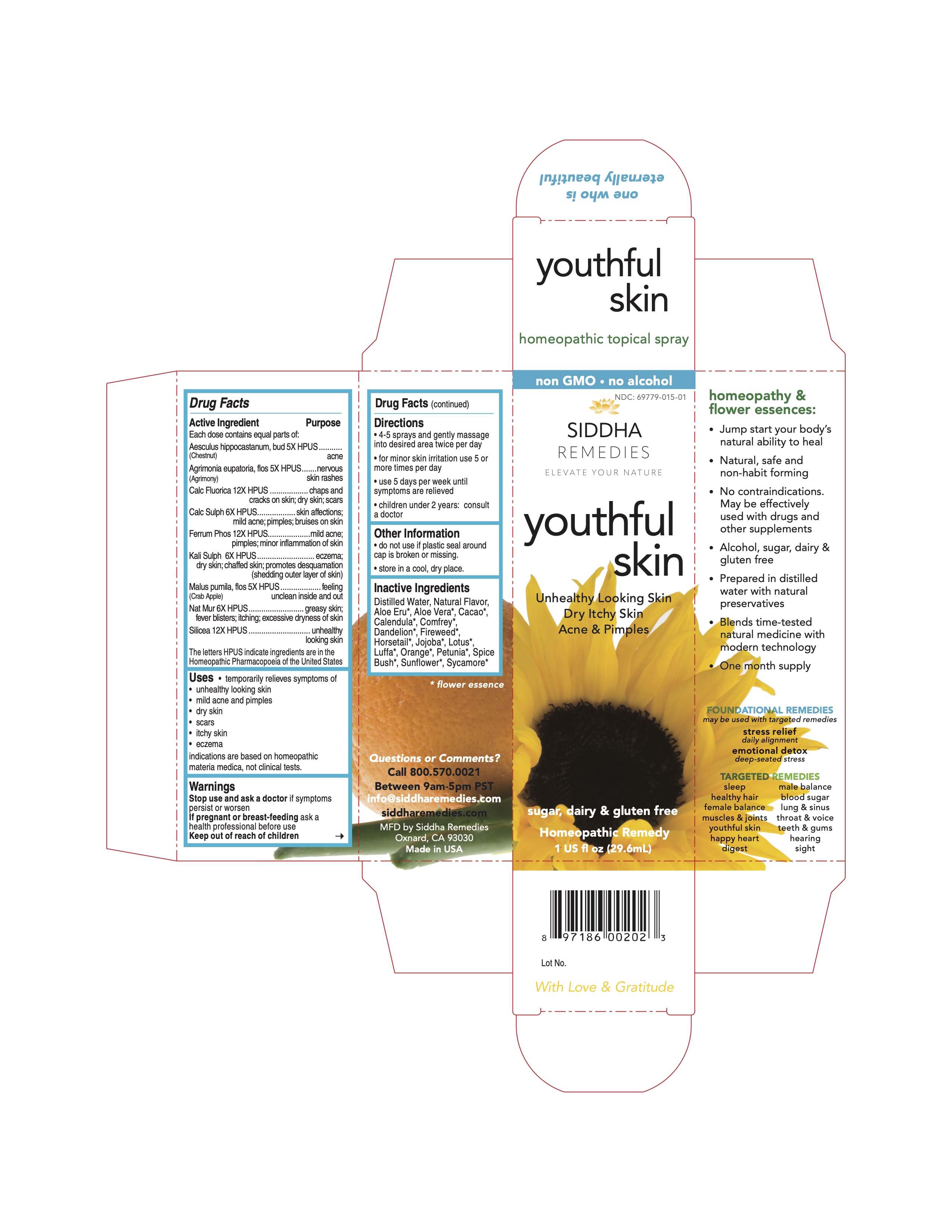 DRUG LABEL: youthful skin
NDC: 69779-015 | Form: SPRAY
Manufacturer: Siddha Flower Essences LLC
Category: homeopathic | Type: HUMAN OTC DRUG LABEL
Date: 20251231

ACTIVE INGREDIENTS: HORSE CHESTNUT 5 [hp_X]/29.6 mL; AGRIMONIA EUPATORIA FLOWER 5 [hp_X]/29.6 mL; CALCIUM FLUORIDE 12 [hp_X]/29.6 mL; CALCIUM SULFATE ANHYDROUS 6 [hp_X]/29.6 mL; FERROSOFERRIC PHOSPHATE 12 [hp_X]/29.6 mL; POTASSIUM SULFATE 6 [hp_X]/29.6 mL; MALUS DOMESTICA FLOWER 5 [hp_X]/29.6 mL; SODIUM CHLORIDE 6 [hp_X]/29.6 mL; SILICON DIOXIDE 12 [hp_X]/29.6 mL
INACTIVE INGREDIENTS: WATER; ALOE VERA FLOWER; COCOA; CALENDULA OFFICINALIS FLOWERING TOP; TARAXACUM OFFICINALE FLOWERING TOP; EPILOBIUM ANGUSTIFOLIUM FLOWERING TOP; EQUISETUM HYEMALE; NELUMBO NUCIFERA FLOWER; CITRUS SINENSIS FLOWER; HELIANTHUS ANNUUS FLOWERING TOP

Drug Fact

Active Ingredient

Each dose contains equal parts of:

Aesculus hippocastanum, bud (Chestnut Bud) 5X HPUS
Agrimonia eupatoria, flos (Agrimony) 5X HPUS
Calc Fluorica 12X HPUS
Ferrum Phos 12X HPUS
Kali Sulph 6X HPUS
Malus pumila, flos (Crab Apple) 5X HPUS
Nat Mur 6X HPUS
Silicea 12X HPUS

Purpose

Each dose contains equal parts of:
Aesculus hippocastanum, bud (Chestnut Bud) 5X HPUS......acne
Agrimonia eupatoria, flos (Agrimony) 5X HPUS...................nervous skin rashes
Calc Fluorica 12X HPUS...................................................chaps and cracks on skin; dry skin; scars
Ferrum Phos 12X HPUS...................................................skin affections; mild acne; pimples; bruises on skin
Kali Sulph 6X HPUS.........................................................mild acne; pimples; minor inflammation of skin
Malus pumila, flos (Crab Apple) 5X HPUS..........................feeling unclean inside and out
Nat Mur 6X HPUS............................................................greasy skin, fever blister; itching; excessive dryness of skin
Silicea 12X HPUS............................................................unhealthy looking skin
The letters HPUS indicate ingredients are in the Homeopathic Pharmacopoeia of the United States.

Uses

- temporarily relieves symptoms of
- unhealthy looking skin
- mild acne and pimples
- dry skin
- scars
- itchy skin
- eczema

indications are based on homeopathic materia medica, not clinical tests.

Uses

Stop use and ask a doctor if symptoms persist or worsen

PREGNANCY OR BREAST FEEDING

If pregnant or breast-feeding ask a health professional before use

Keep out of reach of children

Directions

- 4-5 sprays and gently massage into desired area twice per day
- for minor skin irritation use 5 or more times per day
- use 5 days per week until symptoms are relieved
- children under 2 years: consult a doctor

Other Information

- do not use if plastic seal around cap is broken or missing.
- store in a cool, dry place.

Inactive Ingredients

Purified Water, Natural Flavor, Aloe Eru*, Aloe Vera*, Cacao*, Calendula*, Comfrey*, Dandelion*, Fireweed*, Horsetail*, Jojoba*, Lotus*, Luffa*, Orange*, Petunia*, Spice Bush*, Sunflower*, Sycamore*

*flower essence

Questions or Comments?
Call 800.570.0021
Between 9am-5pm PST
info@siddhaflowers.com
siddhaflowers.com
MFG by Siddha Flower Essences
Oxnard, CA 93030
Made in USA

Side Panel

homeopathy and flower essences:

- Jump start your body's natural ability to heal
- Natural, safe and non-habit forming
- No contraindications. May be effectively used with drugs and other supplements
- Alcohol, sugar, dairy and gluten free
- Prepared in purified water with natural preservatives
- Blends time-tested natural medicine with modern technology
- One month supply

FOUNDATIONAL REMEDIES
may be used with targeted remedies
stress relief
daily alignment
emotional detox
deep-seated stress
TARGETED REMEDIES
sleep male balance
healthy hair blood sugar
female balance lung and sinus
muscles and joints throat and voice
youthful skin teeth and gums
happy heart hearing
digestion sight

Principal Display Panel

non GMO - no alcohol
siddha cell salts + flower essences
youthful skin
Unhealthy Looking Skin
Dry Itchy Skin
Acne and Pimples
sugar, dairy and gluten free
Homeopathic Remedy
1 US fl oz (29.6mL)